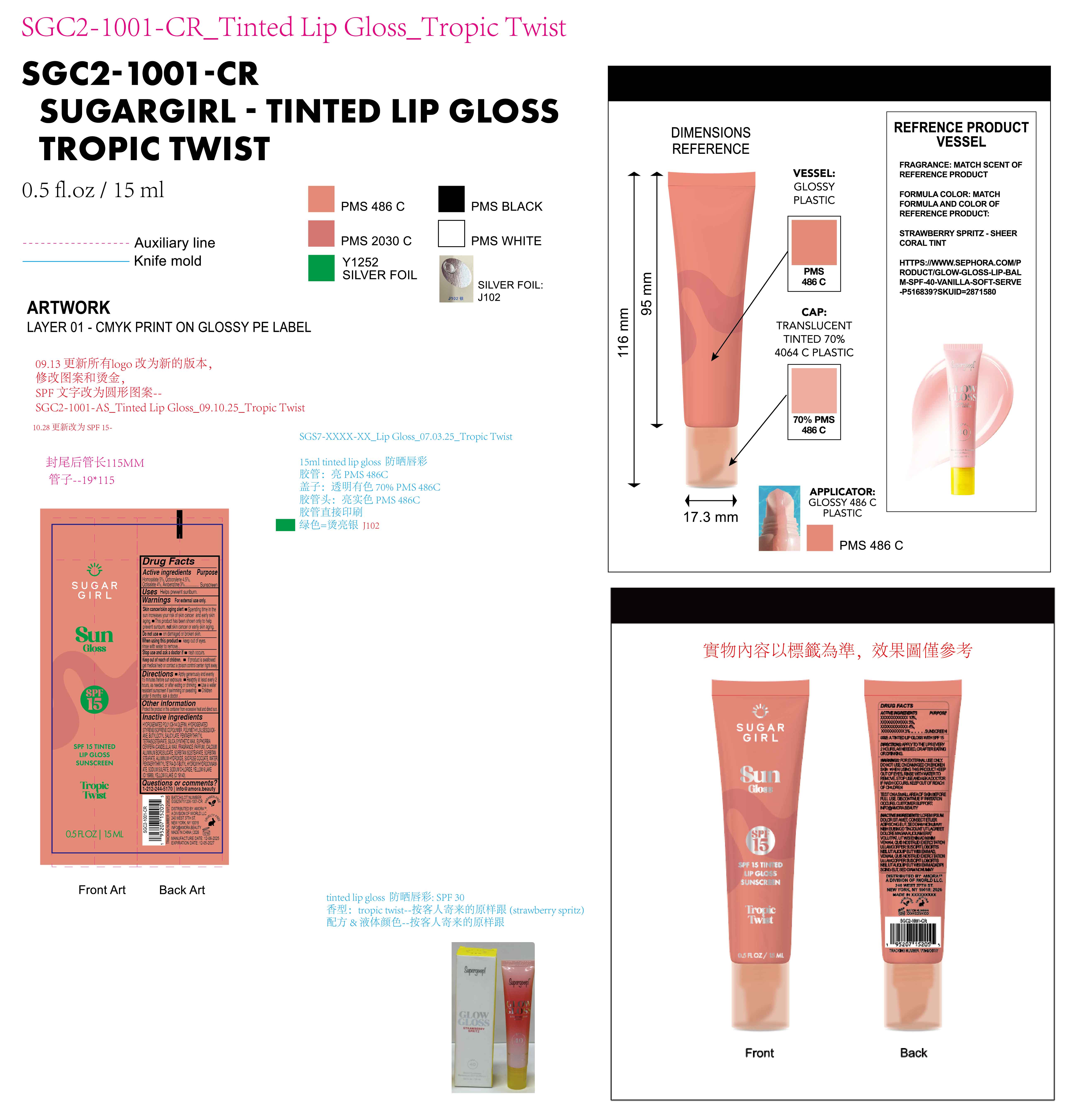 DRUG LABEL: Sugargirl sun gloss SPF15  tinted lip gloss Sunscreen Tropic Twist
NDC: 85161-153 | Form: GEL
Manufacturer: Longway Technology(Guangzhou)Co.,Ltd.
Category: otc | Type: HUMAN OTC DRUG LABEL
Date: 20251204

ACTIVE INGREDIENTS: HOMOSALATE 0.05 g/1 mL; AVOBENZONE 0.03 g/1 mL; OCTOCRYLENE 0.045 g/1 mL; OCTISALATE 0.04 g/1 mL
INACTIVE INGREDIENTS: POLYMETHYLSILSESQUIOXANE (11 MICRONS); CI 19140; SYNTHETIC WAX (540 MW); SORBITAN STEARATE; ALUMINUM HYDROXIDE; SILICA; SORBITAN ISOSTEARATE; WATER; CI 15985; SUCROSE COCOATE; PENTAERYTHRITYL TETRAISOSTEARATE; FRAGRANCE 13576; CALCIUM ALUMINUM BOROSILICATE; STYRENE/ISOPRENE COPOLYMER (28:72; 210000 MW); PENTAERYTHRITYL TETRA-DI-T-BUTYL HYDROXYHYDROCINNAMATE; HYDROGENATED POLY(C6-14 OLEFIN; 4 CST); BUTYLOCTYL SALICYLATE; EUPHORBIA CERIFERA (CANDELILLA) WAX; SODIUM SULFATE; SODIUM CHLORIDE

ACTIVE INGREDIENT

Homosalate 5%, Octocrylene 4.5%, Octisalate 4% , Avobenzone 3%

KEEP OUT OF REACH OF CHILDREN

lf product is swallowed get medical help or contact a poison control center right away

QUESTIONS

1-212-244-5170 info@amora.beauty

OTHER SAFETY INFORMATION

Protect tne product in this container from excessive heat and dlrect sunl

INDICATIONS AND USAGE

Helps prevent sunburn.

DOSAGE AND ADMINISTRATION

Apply generously and evenly15 minutes before sun exposure.

Reapply at least every 2hours, as needed. or after eating or drinking.

Use a water resistant sunscreen if swimming or sweating.

Chidren under 6 months. ask a doctor.

Warnings

For external use only.
Skin cancer/skin aging alert.

Spending time in the sun increases your risk of skin cancer and early skin aging.

This product has been shown only to help prevent sunburn, not skin cancer or early skin aging.

Do not use on damaged or broken skin.

When using this product . keep out of eyes. rinse with water to remove.

Stop use and ask a doctor if rash occurs.

Keep out of reach of children. lf product is swallowed get medical help or contact a poison control center right away

PURPOSE

Sunscreen

INACTIVE INGREDIENT

HYDROGENATED POLY(C6-14 OLEFIN), HYDROGENATED STYRENE/ISOPRENE COPOLYMER, POLYMETHYLSILSESQUIOXANE, BUTYLOCTYL SALICYLATE, PENTAERYTHRITYL TETRAISOSTEARATE, SILICA, SYNTHETIC WAX, EUPHORBIA CERIFERA (CANDELILLA) WAX, FRAGRANCE (PARFUM), CALCIUM ALUMINUM BOROSILICATE, SORBITAN ISOSTEARATE, SORBITAN STEARATE, ALUMINUM HYDROXIDE, SUCROSE COCOATE, WATER, PENTAERYTHRITYL TETRA-DI-T-BUTYL HYDROXYHYDROCINNAMATE, SODIUM SULFATE, SODIUM CHLORIDE, YELLOW NO. 6 LAKE (CI 15985), YELLOW 5 LAKE(CI 19140)